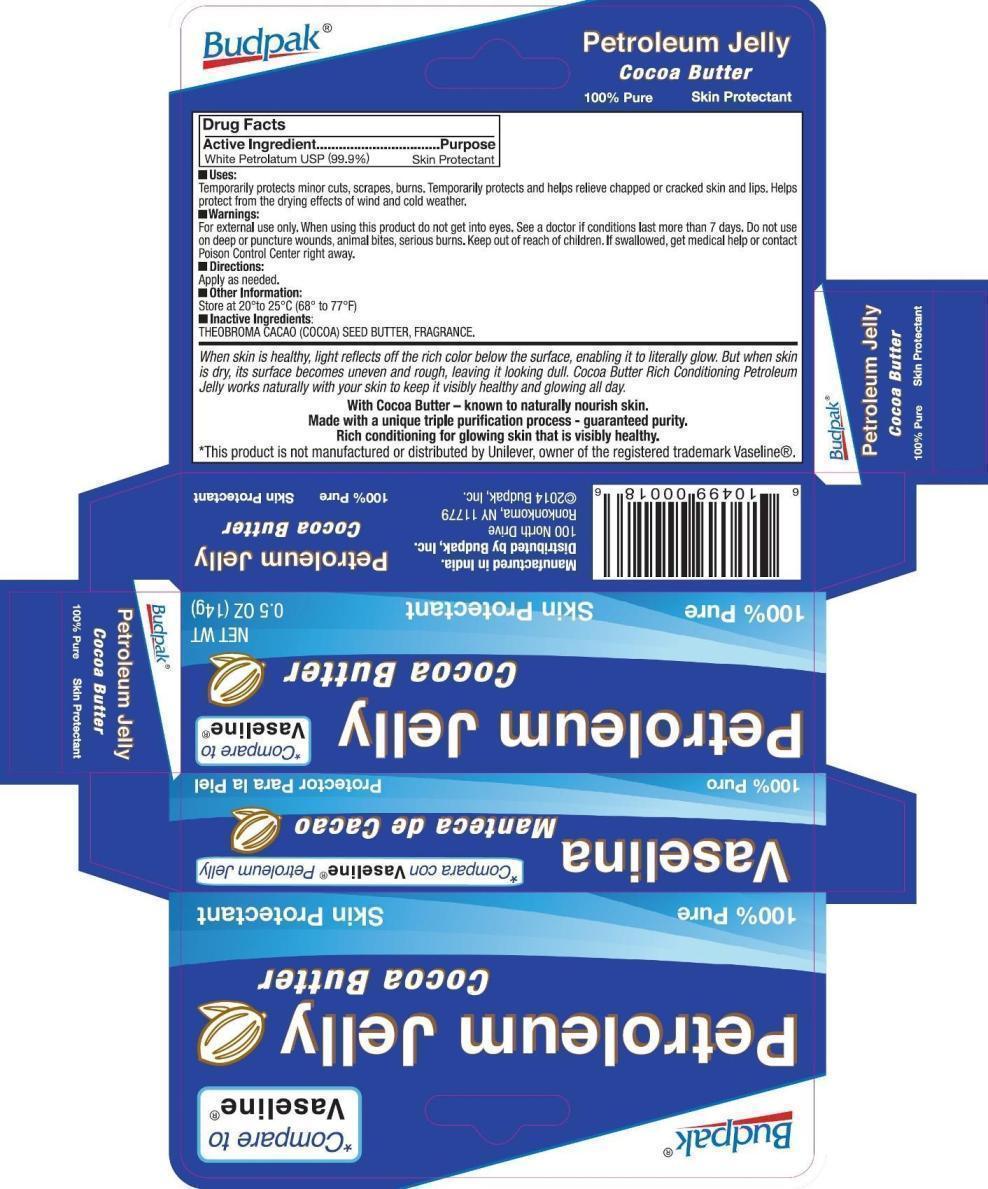 DRUG LABEL: Budpak Petroleum Cocoa Butter
NDC: 27293-029 | Form: JELLY
Manufacturer: Budpak Inc. 
Category: otc | Type: HUMAN OTC DRUG LABEL
Date: 20140214

ACTIVE INGREDIENTS: PETROLATUM 99.9 g/100 g
INACTIVE INGREDIENTS: COCOA BUTTER

Budpak Petroleum Cocoa Butter Jelly

Active Ingredient

White Petrolatum USP 99.9%

Purpose

Skin Protectant

Uses

Temporarily protects minor cuts, scrapes, burns. Temporarily protects and helps relieve chapped or cracked skin and lips. Helps protect from the drying effects of wind and cold weather.

Warnings

For external use only.

When using this product do not get into eyes

STOP USE

See a doctor if condition lasts more than 7 days.

Do not use on deep or puncture wounds, animal bites, serious burns.

Keep out of reach of children.

If swallowed, get medical help or contact Poison Control Center right away.

Directions

Apply as needed.

Other Information

Store at 20°to 25°C (68° to 77°F).

Inactive Ingredients

Theobroma Cacao (Cocoa) Seed Butter, Fragrance.

PRINCIPAL DISPLAY PANEL

Budpak Petroleum Cocoa Butter Jelly

White Petrolatum 99.9%

NET WT 0.5 OZ (14 g)